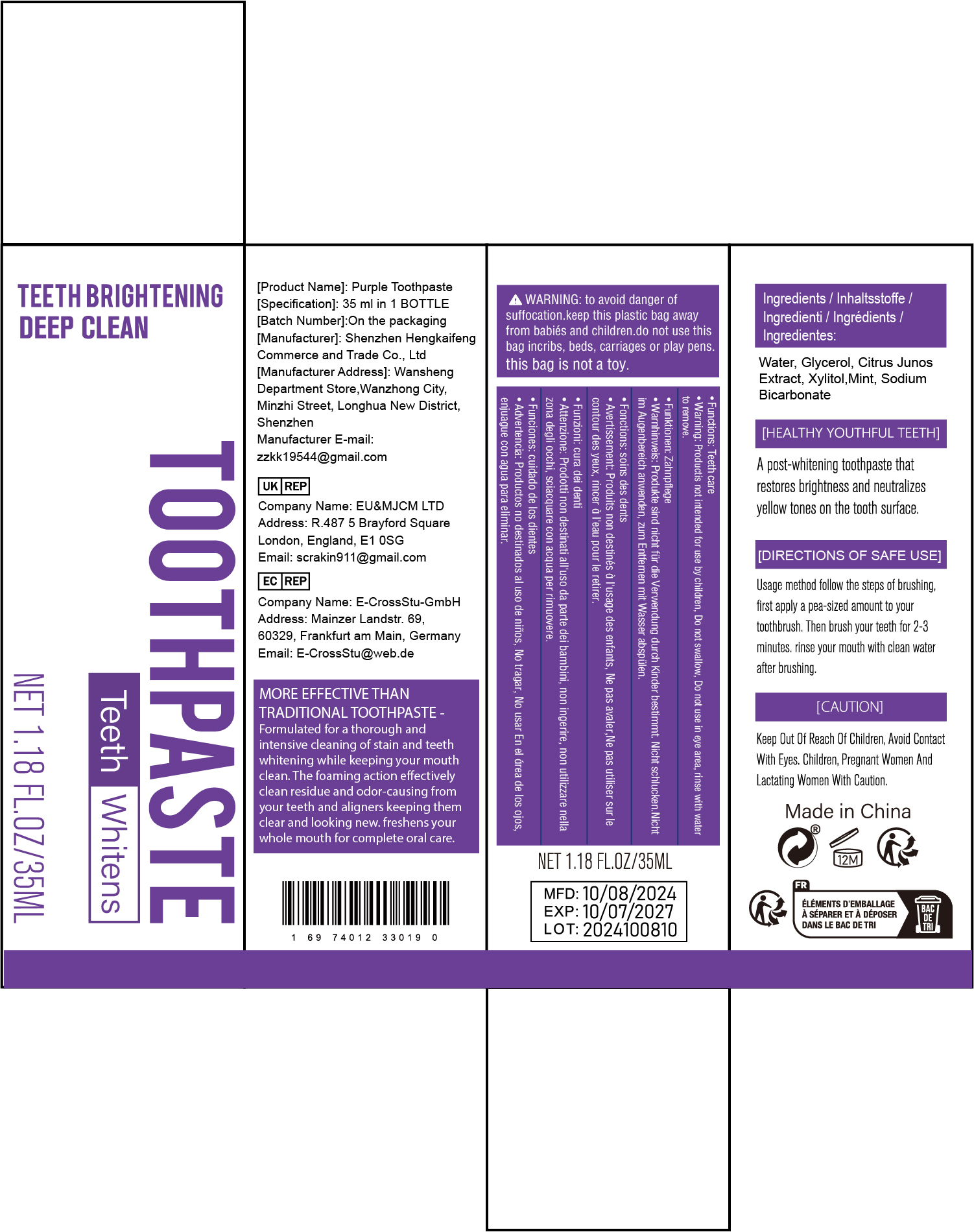 DRUG LABEL: PurpleToothpaste
NDC: 84117-036 | Form: LOTION
Manufacturer: Shenzhen Hengkaifeng Commerce and Trade Co., Ltd
Category: otc | Type: HUMAN OTC DRUG LABEL
Date: 20241021

ACTIVE INGREDIENTS: XYLITOL 20 mg/100 mL
INACTIVE INGREDIENTS: WATER

ACTIVE INGREDIENT

Xylitol

Purpose

Teeth Whitening

Use

Enhance your teeth cleaning routine with the teeth whitening .
The powerful formula works to care for teeth and gums, remove
plaque and tartar, gently lift stains and freshen breath for an overall
deep clean.

Warnings

WARNING: to avoid danger of suffocation. keep this plastic bag
away from babiés and children.do not use this bag incribs, beds,
carriages or play pens.this bag is not a toy.

Keep Out Of Reach Of Children,this is not a toy

Directions Of Safe Use:

Easy to use anytime, anywhere, simply squeeze an appropriate amount
of teeth powder dips your toothbrush, gently brush your teeth for 2
minutes, and then rinse your mouth thoroughly with water. Take it
with you anywhere, anytime, so you can easily enjoy the benefits of
whitening!

Inactive ingredients

Water, Glycerol, Citrus Junos Extract,Mint, Sodium Bicarbonate